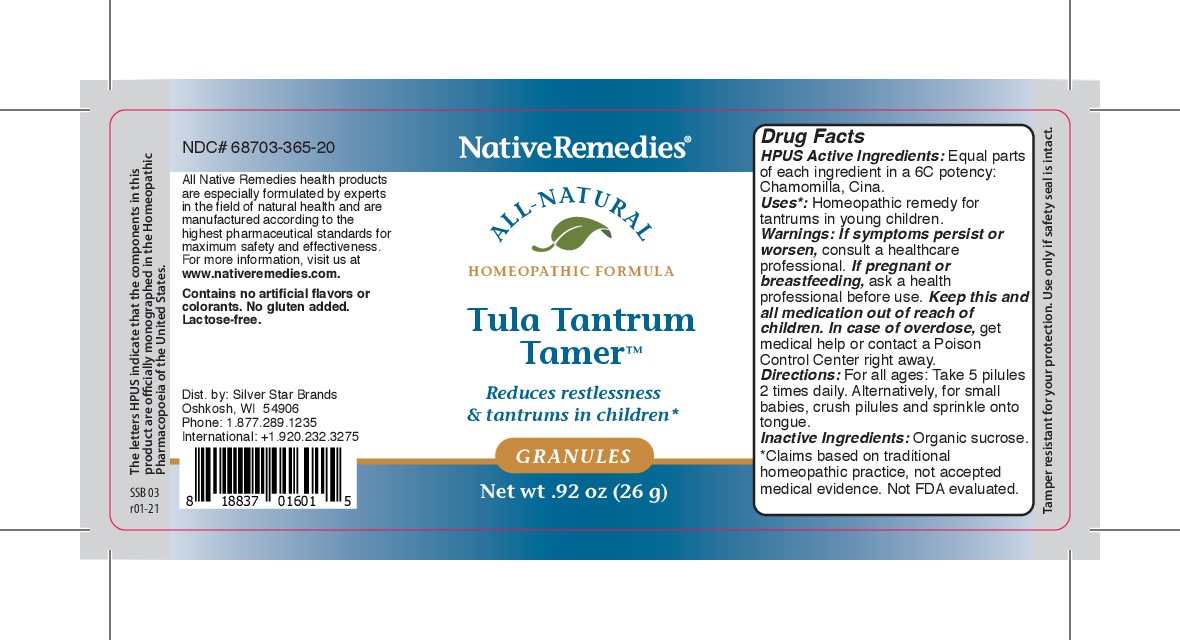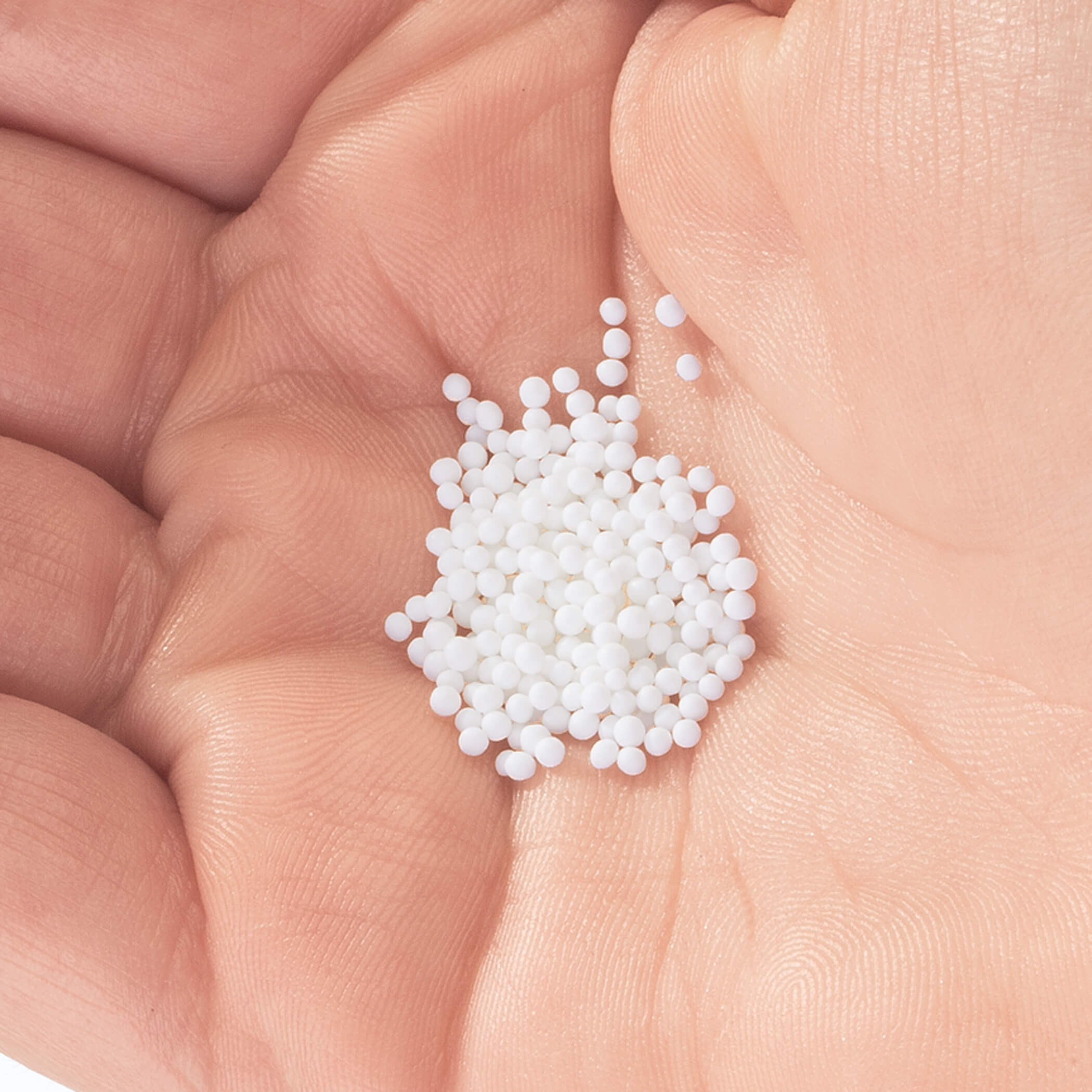 DRUG LABEL: Tula Tantrum Tamer
NDC: 68703-365 | Form: PELLET
Manufacturer: Silver Star Brands
Category: homeopathic | Type: HUMAN OTC DRUG LABEL
Date: 20250101

ACTIVE INGREDIENTS: ARTEMISIA CINA FLOWER 6 [hp_C]/26 g; MATRICARIA RECUTITA 6 [hp_C]/26 g
INACTIVE INGREDIENTS: SUCROSE

NativeRemedies® Tula Tantrum Tamer™ Granules

HPUS Active Ingredients: Equal parts of each ingredient in a 6C potency: Chamomilla, Cina.

Uses*

Uses*: Homeopathic remedy for tantrums in young children

* Claims based on traditional homeopathic practice, not accepted medical evidence. Not FDA evaluated.

Warnings

Warnings: If symptoms persist or worsen, consult a healthcare professional. If pregnant or breastfeeding, ask a health professional before use. Keep this and all medication out of reach of children. In case of overdose, get medical help or contact a Poison Control Center right away.

Directions

Directions For all ages: Take 5 pilules 2 times daily. Alternatively, for small babies, crush pilules onto tongue.

OTHER SAFETY INFORMATION

Contains no artificial flavors or colorants. No gluten added. Lactose-free.

Tamper resistant for your protection. Use only if safetey seal is in tact.

Inactive Ingredients

Inactive Ingredients: Organic Sucrose

KEEP OUT OF REACH OF CHILDREN

Keep this and all medication out of reach of children.

PREGNANCY OR BREAST FEEDING

If pregnant or breastfeeding, ask a health professional before use.

PURPOSE

Reduces restlessness & tantrums in children

*Claims based on traditional homeopathic practice, not accepted medical evidence. Not FDA evaluated.